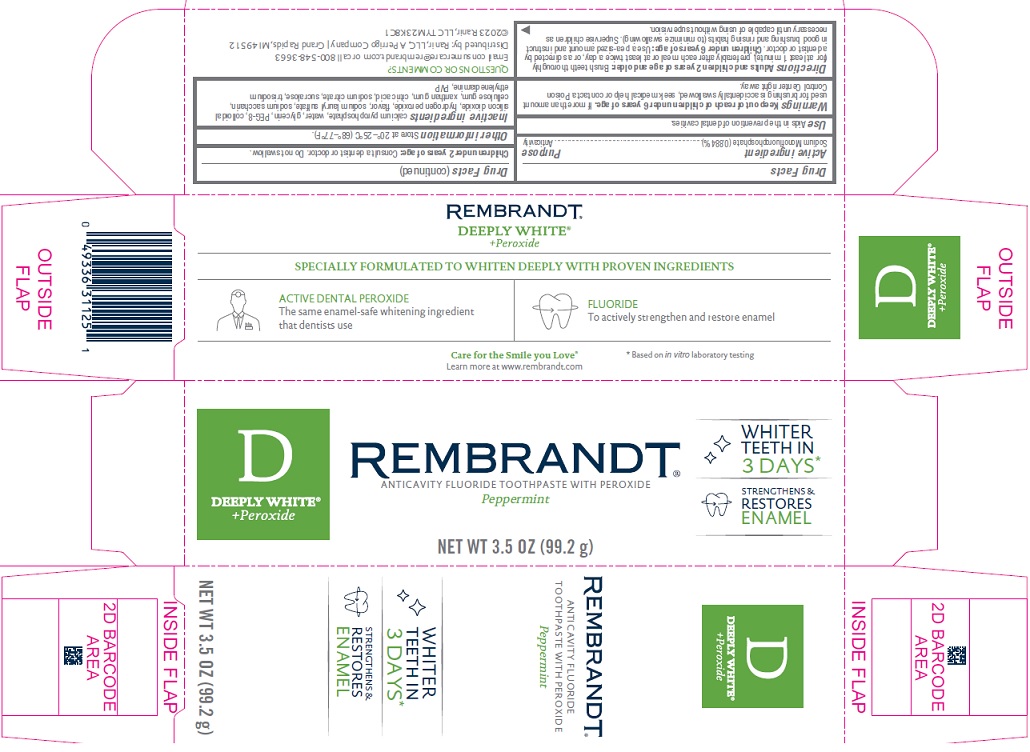 DRUG LABEL: Rembrandt Deeply White Plus Peroxide
NDC: 66923-123 | Form: PASTE, DENTIFRICE
Manufacturer: Ranir LLC
Category: otc | Type: HUMAN OTC DRUG LABEL
Date: 20241120

ACTIVE INGREDIENTS: SODIUM MONOFLUOROPHOSPHATE 0.884 g/100 g
INACTIVE INGREDIENTS: CALCIUM PYROPHOSPHATE; WATER; GLYCERIN; POLYETHYLENE GLYCOL 400; SILICON DIOXIDE; HYDROGEN PEROXIDE; SODIUM LAURYL SULFATE; SACCHARIN SODIUM; CARBOXYMETHYLCELLULOSE SODIUM, UNSPECIFIED; XANTHAN GUM; CITRIC ACID MONOHYDRATE; SODIUM CITRATE, UNSPECIFIED FORM; SUCRALOSE; POVIDONE, UNSPECIFIED

Rembrandt D Deeply White® Plus Peroxide Drug Facts

Active ingredient

Sodium Monofluorophosphate (0.884%)

Purpose

Anticavity

Use

Aids in the prevention of dental cavities.

Warnings

Keep out of reach of children under 6 years of age.

If more than amount used for brushing is accidentally swallowed, seek medical help or contact a Poison Control Center right away.

Directions

Adults and children 2 years of age and older: Brush teeth thoroughly (for at least 1 minute), preferable after each meal or at least twice a day, or as directed by a dentist or doctor. Children under 6 years of age: Use a pea-sized amount and instruct in good brushing and rinsing habits (to minimize swallowing). Supervise children as necessary until capable of using without supervision. Children under 2 years of age: Consult a dentist or doctor. Do not swallow.

Other information

Store at 20° - 25°C (68°-77°F).

Inactive ingredients

calcium pyrophosphate, water, glycerin, PEG-8, colloidal silicon dioxide, hydrogen peroxide, flavor, sodium lauryl sulfate, sodium saccharin, cellulose gum, xanthan gum, citric acid, sodium citrate, sucralose, trisodium ethylenediamine, PVP

Package/Label Principal Display Panel

D DEEPLY WHITE® + Peroxide

WHITER TEETH IN 3 DAYS

REMBRANDT®

ANTICAVITY FLUORIDE TOOTHPASTE WITH PEROXIDE

STRENGTHENS & RESTORES ENAMEL

Peppermint

NET WT 3.5 OZ (99.2 g)